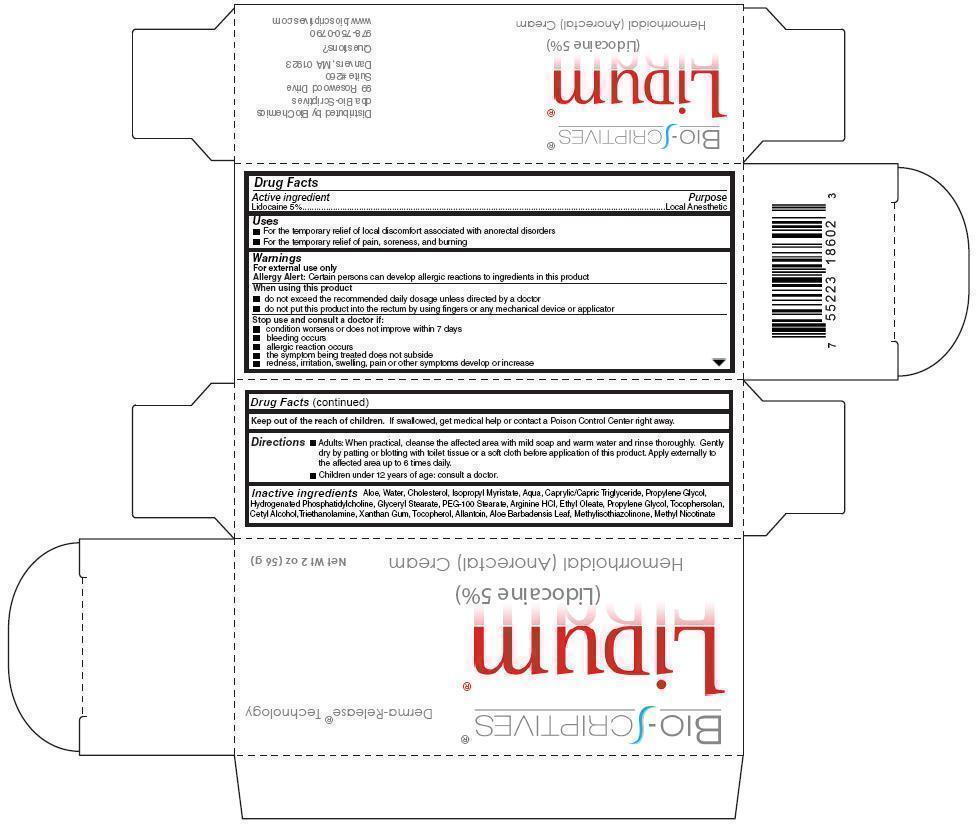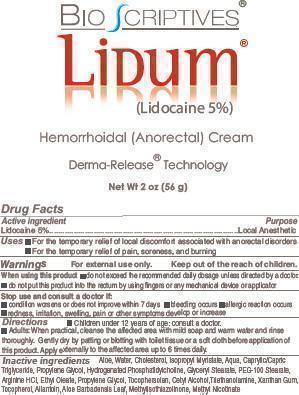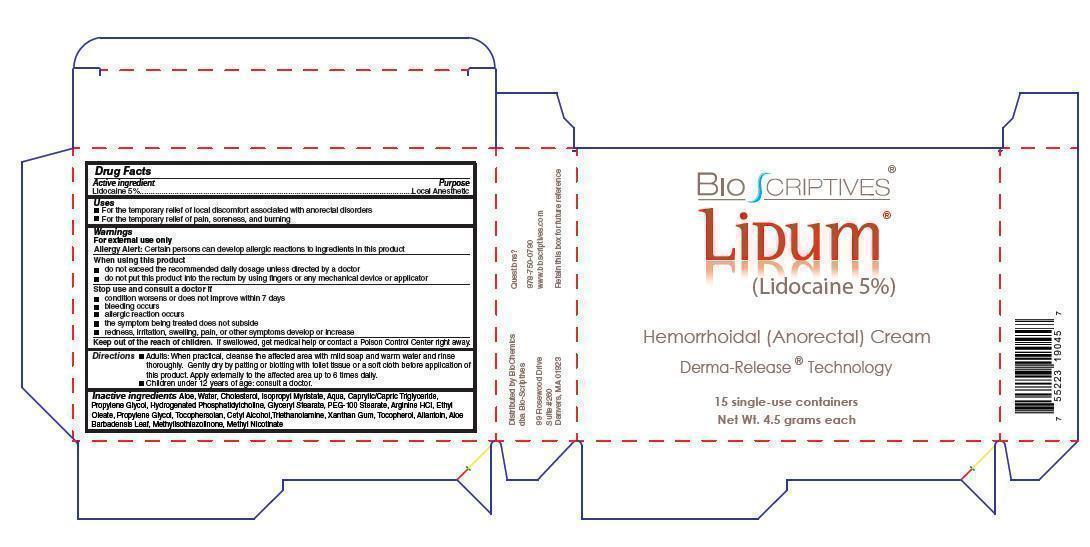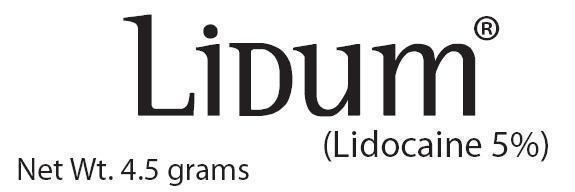 DRUG LABEL: Bio-Scriptives Lidum Hemorroidal (Anorectal)
NDC: 60608-016 | Form: CREAM
Manufacturer: Bio-Scriptives, Inc.
Category: otc | Type: HUMAN OTC DRUG LABEL
Date: 20120309

ACTIVE INGREDIENTS: LIDOCAINE 2.8 g/56 g
INACTIVE INGREDIENTS: ALOE VERA LEAF; WATER; CHOLESTEROL; ISOPROPYL MYRISTATE; MEDIUM-CHAIN TRIGLYCERIDES; HYDROGENATED SOYBEAN LECITHIN; GLYCERYL MONOSTEARATE; POLYETHYLENE GLYCOL; ARGININE HYDROCHLORIDE; ETHYL OLEATE; PROPYLENE GLYCOL; TOCOPHERSOLAN; CETYL ALCOHOL; TROLAMINE; XANTHAN GUM; ALPHA-TOCOPHEROL; ALLANTOIN; METHYLISOTHIAZOLINONE; METHYL NICOTINATE

Bio-Scriptives Lidum (Lidocaine 5%) Hemorroidal (Anorectal) Cream

Active Ingredient

Lidocaine 5%

Purpose

Local Anesthetic

Uses

■ For the temporary relief of local discomfort associated with anorectal disorders

■ For the temporary relief of pain, soreness, and burning.

Warnings

For external use only.

When using this product ■ do not exceed the recommended daily dosage unless directed by a doctor.

■ do not put this product into the rectum by using fingers or any mechanical device or applicator.

Stop use and consult a doctor if:

■ condition worsens or does not improve within 7 days ■ bleeding occurs ■ allergic reaction occurs ■ redness, irritation, swelling, pain or other symptoms develop or increase

Keep out of reach of children.

Directions

■ Children under 12 years of age: consult a doctor. ■ Adults: When practical, cleanse the affected area with mild soap and warm water and rinse thoroughly. Gently dry by patting or blotting with toilet tissue or a soft cloth before application of this product. Apply externally to the affected area up to 6 times daily.

Inactive Ingredients

Aloe, Water, Cholesterol, Isopropyl Mysristate, Aqua, Caprylic/Capric Triglyceride, Propylene Glycol, Hydrogenated Phosphatidylcholine, Glyceryl Stearate, PEG-100 Stearate, Arginine HCI, Ethyl Oleate, Propylene Glycol, Tocophersolan, Cetyl Alcohol, Triethanolamine, Xanthan Gum, Tocopherol, Allantoin, Aloe Barbadensis Leaf, Methylisothiazolinone, Methyl Nicotinate

Package and Lidum Images

+